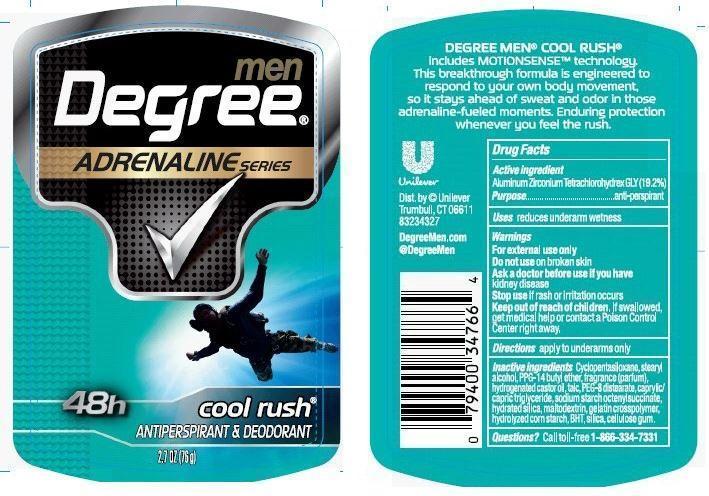 DRUG LABEL: Degree
NDC: 64942-1318 | Form: STICK
Manufacturer: Conopco Inc. d/b/a Unilever
Category: otc | Type: HUMAN OTC DRUG LABEL
Date: 20221205

ACTIVE INGREDIENTS: ALUMINUM ZIRCONIUM TETRACHLOROHYDREX GLY 19.2 g/100 g
INACTIVE INGREDIENTS: CYCLOMETHICONE 5; PPG-14 BUTYL ETHER; STEARYL ALCOHOL; HYDROGENATED CASTOR OIL; PEG-8 DISTEARATE; TALC; STARCH, CORN; BUTYLATED HYDROXYTOLUENE; HYDRATED SILICA; MALTODEXTRIN; SILICON DIOXIDE; CARBOXYMETHYLCELLULOSE SODIUM

Degree Cool Rush antiperspirant deodorant

Active Ingredient

Aluminum Zirconium Tetrachlorohydrex GLY (19.2%)

Purpose
antiperspirant

Uses
reduces underarm wetness

Warnings
For external use only

Do not use on broken skin

Ask a doctor before use if you have kidney disease

Stop use if rash or irritation occurs

Keep out of reach of children. If swallowed, get medical help or contact a Poison Control Center right away.

Directions

apply to underarms only

INACTIVE INGREDIENT

Inactive ingredients: Cyclopentasiloxane, Stearyl Alcohol, PPG-14 Butyl Ether, Fragrance (Parfum), Hydrogenated Castor Oil, Talc, PEG-8 Distearate, Caprylic/Capric Triglyceride, Sodium Starch Octenylsuccinate, Hydrated Silica, Maltodextrin, Gelatin Crosspolymer, Hydrolyzed Corn Starch, BHT, Silica, Cellulose Gum

Questions?
Call toll-free 1-866-334-7331